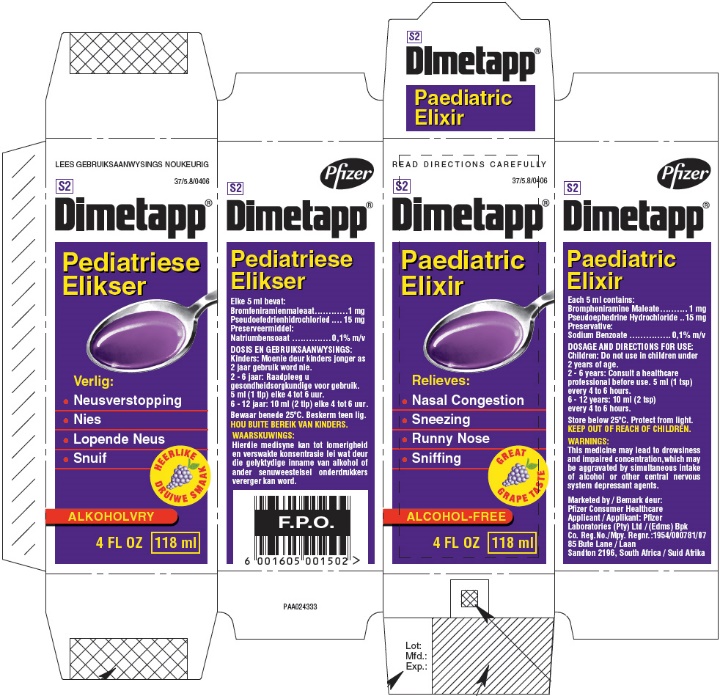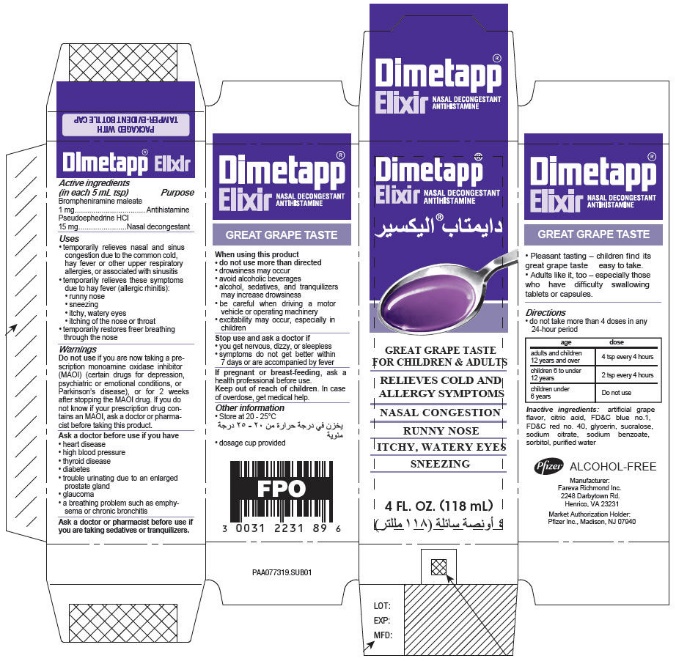 DRUG LABEL: Dimetapp Paediatric
NDC: 0031-2251 | Form: ELIXIR
Manufacturer: Haleon US Holdings LLC
Category: otc | Type: HUMAN OTC DRUG LABEL
Date: 20240424

ACTIVE INGREDIENTS: BROMPHENIRAMINE MALEATE 1 mg/5 mL; PSEUDOEPHEDRINE HYDROCHLORIDE 15 mg/5 mL
INACTIVE INGREDIENTS: SODIUM BENZOATE; SORBITOL; GLYCERIN; ANHYDROUS CITRIC ACID; TRISODIUM CITRATE DIHYDRATE; SUCRALOSE; FD&C BLUE NO. 1; WATER; FD&C RED NO. 40

Dimetapp®Paediatric Elixir

PRINCIPAL DISPLAY PANEL - 118 ml Bottle Carton

READ DIRECTIONS CAREFULLY

37/5.8/0406

S2

Dimetapp®

Paediatric
Elixir

Relieves:

1. Nasal Congestion
2. Sneezing
3. Runny Nose
4. Sniffing

GREAT
GRAPE TASTE

ALCOHOL-FREE

4 FL OZ 118 ml

PRINCIPAL DISPLAY PANEL - 118 mL Bottle Carton - Adult

Dimetapp®
Elixir
NASAL DECONGESTANT
ANTIHISTAMINE

GREAT GRAPE TASTE
FOR CHILDREN & ADULTS

RELIEVES COLD AND
ALLERGY SYMPTOMS

NASAL CONGESTION

RUNNY NOSE

ITCHY, WATERY EYES

SNEEZING

4 FL. OZ. (118 mL)